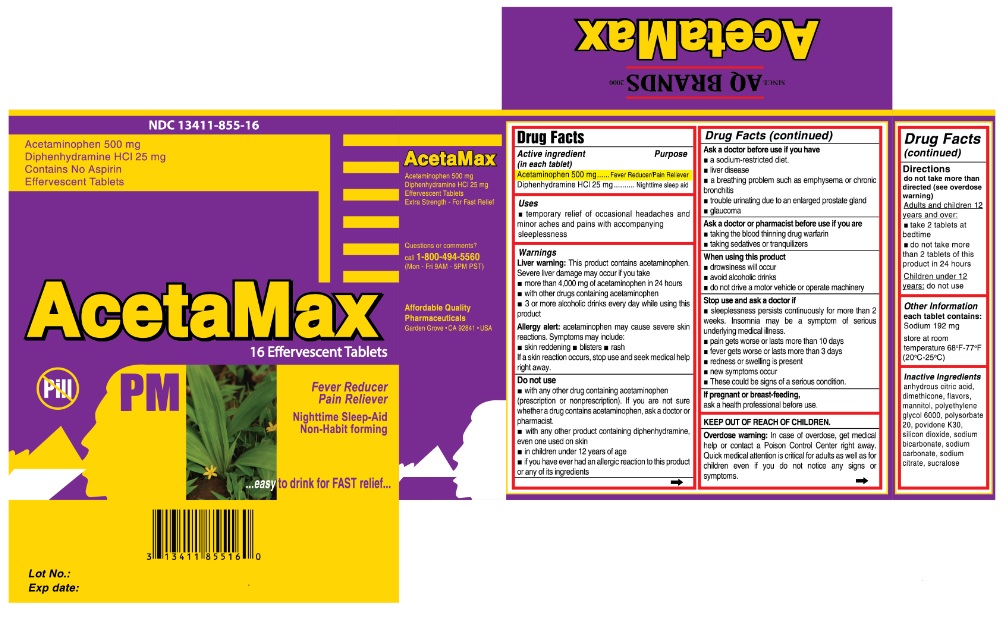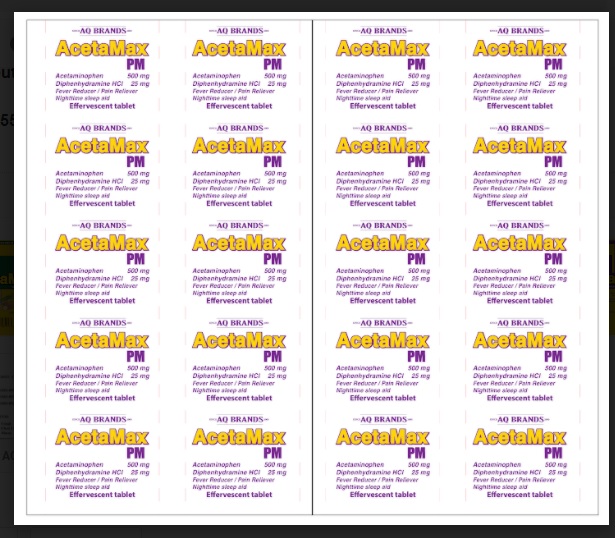 DRUG LABEL: AcetaMax PM
NDC: 13411-855 | Form: TABLET, EFFERVESCENT
Manufacturer: Advanced Pharmaceutical Services, Inc. Dba Affordable Quality Pharmaceuticals
Category: otc | Type: HUMAN OTC DRUG LABEL
Date: 20200831

ACTIVE INGREDIENTS: ACETAMINOPHEN 500 mg/1 1; DIPHENHYDRAMINE 25 mg/1 1
INACTIVE INGREDIENTS: ANHYDROUS CITRIC ACID; DIMETHICONE; MANNITOL; POLYETHYLENE GLYCOL 6000; POLYSORBATE 20; POVIDONE K30; SILICON DIOXIDE; SODIUM BICARBONATE; SODIUM CARBONATE; SODIUM CITRATE; SUCRALOSE

AcetaMax PM

Active Ingredients

Acetaminophen 500 mg
Diphenhydramine HCl 25 mg

Purpose

- Fever Reducer/Pain Reliever
- Nighttime sleep aid

Uses

- temporary relief of occasional headaches and minor aches and pains with accompanying sleeplessness.

Warnings

Liver warning: This product contains acetaminophen. Severe liver damage may occur if you take
• more than 4,000 mg of acetaminophen in 24 hours
• with other drugs containing acetaminophen
• 3 or more alcoholic drinks every day while using this product

Allergy alert: acetaminophen may cause severe skin reactions. Symptoms may include:
• skin reddening

• blisters

• rash

If a skin reaction occurs, stop use and seek medical help right away.

Do not use
• with any other drug containing acetaminophen (prescription or nonprescription). If you are not sure whether a drug contains acetaminophen, ask a doctor or pharmacist.
• with any other product containing diphenhydramine, even one used on skin
• in children under 12 years of age
• if you have ever had an allergic reaction to this product or any of its ingredients

Ask a doctor before use if you have
• a sodium-restricted diet.
• liver disease
• a breathing problem such as emphysema or chronic bronchitis
• trouble urinating due to an enlarged prostate gland
• glaucoma

Ask a doctor or pharmacist before use if you are
• taking the blood thinning drug warfarin
• taking sedatives or tranquilizers

When using this product
• drowsiness will occur
• avoid alcoholic drinks
• do not drive a motor vehicle or operate machinery

Stop use and ask a doctor if

• sleeplessness persists continuously for more than 2 weeks. Insomnia may be a symptom of serious underlying medical illness.
• pain gets worse or lasts more than 10 days
• fever gets worse or lasts more than 3 days
• redness or swelling is present
• new symptoms occur
• These could be signs of a serious condition.

If pregnant or breast-feeding,
ask a health professional before use.

Overdose warning: In case of overdose, get medical help or contact a Poison Control Center right away. Quick medical attention is critical for adults as well as for children even if you do not notice any signs or symptoms.

Directions

Do not take more than directed (see overdose warning)
Adults and children 12 years and over:
• take 2 tablets fully dissolved in 8oz of water at bedtime.
• do not take more than 2 tablets of this product in 24 hours

Children under 12 years: do not use

Other information

Each tablet contains:
Sodium 192 mg
Store at room temperature 68 F-77 F (20oC-25oC)

Inactive Ingredients

anhydrous citric acid, dimethicone, flavors, mannitol, polyethylene glycol 6000, polysorbate 20, povidone K30, silicon dioxide, sodium bicarbonate, sodium carbonate, sodium citrate, sucralose